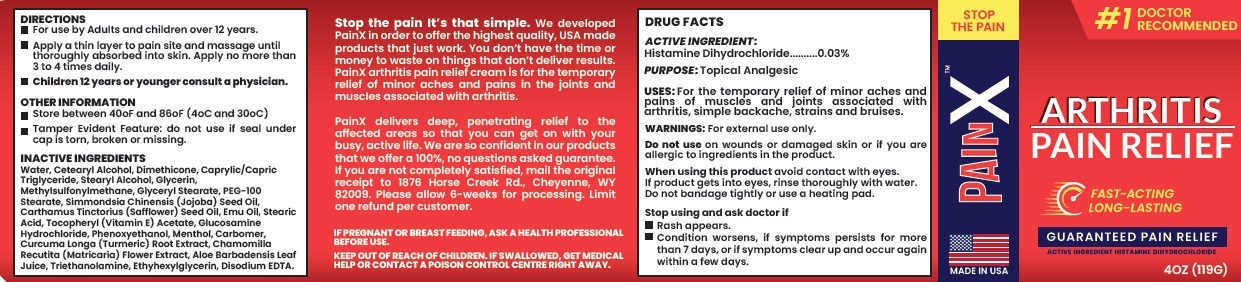 DRUG LABEL: ARTHRITIS PAIN RELIEF
NDC: 83041-101 | Form: CREAM
Manufacturer: PainX LLC
Category: otc | Type: HUMAN OTC DRUG LABEL
Date: 20221107

ACTIVE INGREDIENTS: HISTAMINE DIHYDROCHLORIDE 0.03 g/100 g
INACTIVE INGREDIENTS: .ALPHA.-TOCOPHEROL ACETATE; MATRICARIA CHAMOMILLA FLOWERING TOP; JOJOBA OIL; MEDIUM-CHAIN TRIGLYCERIDES; STEARIC ACID; PHENOXYETHANOL; STEARYL ALCOHOL; DIMETHICONE; GLUCOSAMINE HYDROCHLORIDE; MENTHOL; CARBOMER HOMOPOLYMER, UNSPECIFIED TYPE; TURMERIC; TROLAMINE; ETHYLHEXYLGLYCERIN; SAFFLOWER OIL; GLYCERIN; WATER; CETOSTEARYL ALCOHOL; DIMETHYL SULFONE; GLYCERYL MONOSTEARATE; PEG-100 STEARATE; EMU OIL; ALOE VERA LEAF; EDETATE DISODIUM ANHYDROUS

PAINX - ARTHRITIS PAIN RELIEF (83041-101)

ACTIVE INGREDIENT

HISTAMINE DIHYDROCHLORIDE 0.03%

PURPOSE

TOPICAL ANALGESIC

USES

For the temporary relief of minor aches and pains of muscles and joints associated with arthritis, simple backache, strains and bruises.

WARNINGS

For external use only.

Do not use on wounds or damaged skin or if you are allergic to ingredients in the product.

When using this product avoid contact with eyes. If product gets into eyes, rinse thoroughly with water.

Do not bandage tightly or use a heating pad.

Stop using and ask doctor if

- Rash appears.
- Condition worsens, if symptoms persists for more than 7 days, or if symptoms clear up and occur again within a few days.

DIRECTIONS

- For use by Adults and children over 12 years.
- Apply a thin layer to pain site and massage until thoroughly absorbed into skin. Apply no more than 3 to 4 times daily.
- Children 12 years or younger consult a physician.

PREGNANCY

IF PREGNANT OR BREAST FEEDING, ASK A HEALTH PROFESSIONAL BEFORE USE.

KEEP OUT OF REACH OF CHILDREN. IF SWALLOWED, GET MEDICAL HELP OR CONTACT A POISON CONTROL CENTRE RIGHT AWAY.

OTHER INFORMATION

- Store between 40°F and 86°F (4°C and 30°C)
- Tamper Evident Feature: do not use if seal under cap is torn, broken or missing.

INACTIVE INGREDIENTS

Water, Cetearyl Alcohol, Dimethicone, Caprylic/Capric Triglyceride, Stearyl Alcohol, Glycerin, Methylsulfonylmethane, Glyceryl Stearate, PEG-100 Stearate, Simmondsia Chinensis (Jojoba) Seed Oil, Carthamus Tinctorius (Safflower) Seed Oil, Emu Oil, Stearic
Acid, Tocopheryl (Vitamin E) Acetate, Glucosamine Hydrochloride, Phenoxyethanol, Menthol, Carbomer, Curcuma Longa (Turmeric) Root Extract, Chamomilla Recutita (Matricaria) Flower Extract, Aloe Barbadensis Leaf Juice, Triethanolamine, Ethyhexylglycerin, Disodium EDTA.